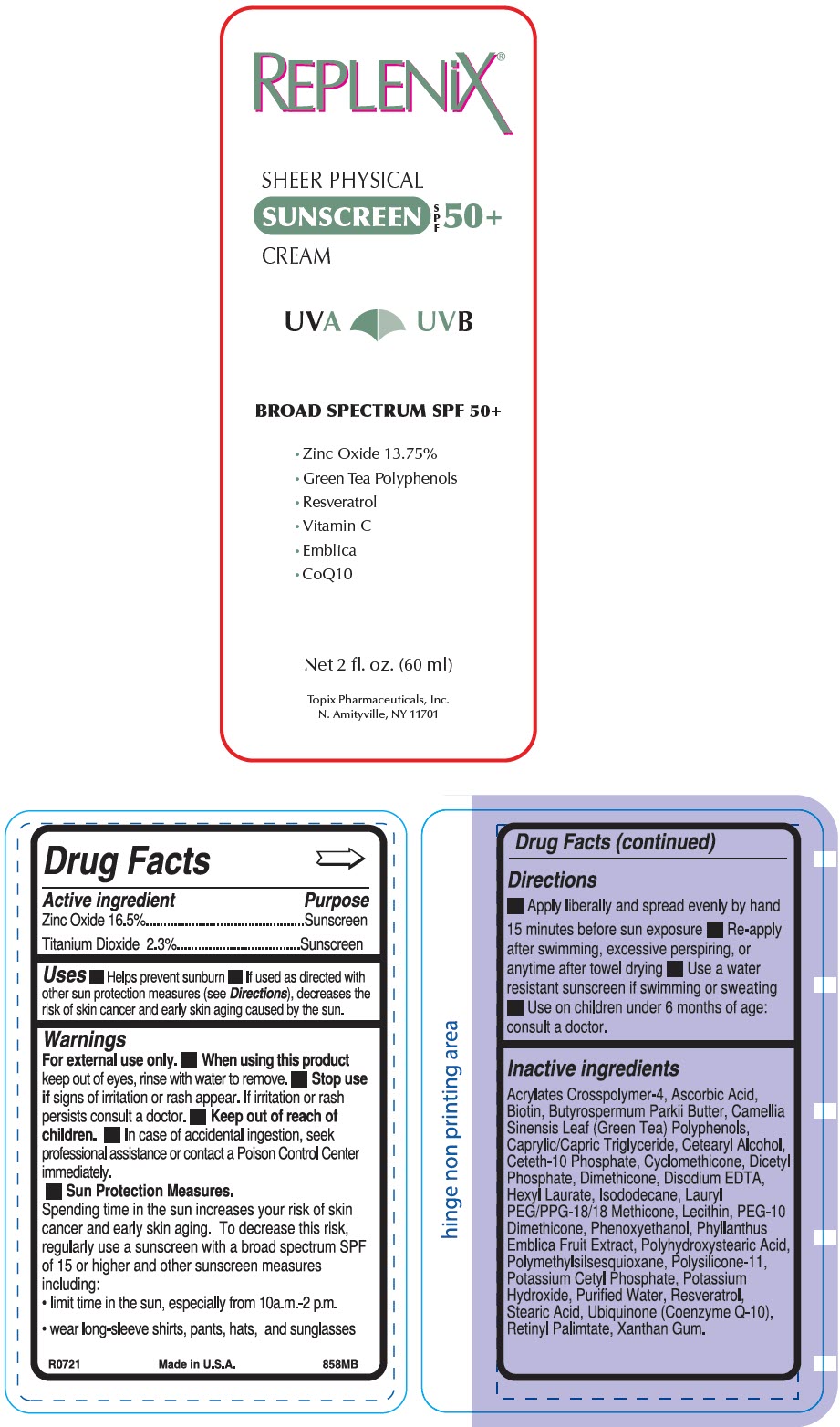 DRUG LABEL: Replenix Sheer
NDC: 51326-858 | Form: CREAM
Manufacturer: Topiderm, Inc.
Category: otc | Type: HUMAN OTC DRUG LABEL
Date: 20240729

ACTIVE INGREDIENTS: ZINC OXIDE 165 mg/1 g; TITANIUM DIOXIDE 23 mg/1 g
INACTIVE INGREDIENTS: ACRYLATES CROSSPOLYMER-4; ASCORBIC ACID; BIOTIN; BUTYROSPERMUM PARKII (SHEA) BUTTER UNSAPONIFIABLES; GREEN TEA LEAF; MEDIUM-CHAIN TRIGLYCERIDES; CETOSTEARYL ALCOHOL; CETETH-10 PHOSPHATE; CYCLOMETHICONE; DIHEXADECYL PHOSPHATE; DIMETHICONE; EDETATE DISODIUM; HEXYL LAURATE; ISODODECANE; LAURYL PEG/PPG-18/18 METHICONE; LECITHIN, SUNFLOWER; PEG-10 DIMETHICONE (200 CST); PHENOXYETHANOL; PHYLLANTHUS EMBLICA FRUIT; POLYHYDROXYSTEARIC ACID (2300 MW); POLYMETHYLSILSESQUIOXANE (11 MICRONS); DIMETHICONE/VINYL DIMETHICONE CROSSPOLYMER (SOFT PARTICLE); POTASSIUM CETYL PHOSPHATE; POTASSIUM HYDROXIDE; WATER; RESVERATROL; STEARIC ACID; UBIDECARENONE; VITAMIN A PALMITATE

Replenix® Sheer
SPF 50

Drug Facts

ACTIVE INGREDIENT

Active ingredient | Purpose
Zinc Oxide 16.5% | Sunscreen
Titanium Dioxide 2.3% | Sunscreen

Uses

- Helps prevent sunburn
- If used as directed with other sun protection measures (see Directions), decreases the risk of skin cancer and early skin aging caused by the sun.

Warnings

For external use only.

- When using this product keep out of eyes, rinse with water to remove.

- Stop use if signs of irritation or rash appear. If irritation or rash persists consult a doctor.

- Keep out of reach of children.
- In case of accidental ingestion, seek professional assistance or contact a Poison Control Center immediately.

- Sun Protection Measures.
  Spending time in the sun increases your risk of skin cancer and early skin aging. To decrease this risk, regularly use a sunscreen with a broad spectrum SPF of 15 or higher and other sunscreen measures including:
  - limit time in the sun, especially from 10a.m.-2 p.m.
  - wear long-sleeve shirts, pants, hats, and sunglasses

Directions

- Apply liberally and spread evenly by hand 15 minutes before sun exposure
- Re-apply after swimming, excessive perspiring, or anytime after towel drying
- Use a water resistant sunscreen if swimming or sweating
- Use on children under 6 months of age: consult a doctor.

Inactive ingredients

Acrylates Crosspolymer-4, Ascorbic Acid, Biotin, Butyrospermum Parkii Butter, Camellia Sinensis Leaf (Green Tea) Polyphenols, Caprylic/Capric Triglyceride, Cetearyl Alcohol, Ceteth-10 Phosphate, Cyclomethicone, Dicetyl Phosphate, Dimethicone, Disodium EDTA, Hexyl Laurate, Isododecane, Lauryl PEG/PPG-18/18 Methicone, Lecithin, PEG-10 Dimethicone, Phenoxyethanol, Phyllanthus Emblica Fruit Extract, Polyhydroxystearic Acid, Polymethylsilsesquioxane, Polysilicone-11, Potassium Cetyl Phosphate, Potassium Hydroxide, Purified Water, Resveratrol, Stearic Acid, Ubiquinone (Coenzyme Q-10), Retinyl Palimtate, Xanthan Gum.

PRINCIPAL DISPLAY PANEL - 60 g Bottle Label

REPLENiX®

SHEER PHYSICAL

SUNSCREEN
SPF
50+
CREAM

UVA UVB

BROAD SPECTRUM SPF 50+

- Zinc Oxide 13.75%
- Green Tea Polyphenols
- Resveratrol
- Vitamin C
- Emblica
- CoQ10

Net 2 fl. oz. (60 ml)

Topix Pharmaceuticals, Inc.
N. Amityville, NY 11701